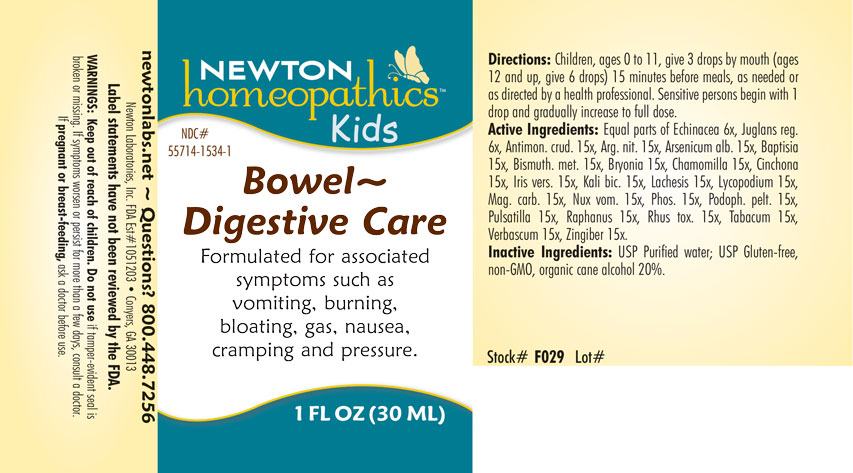 DRUG LABEL: Bowel-Digestive Care
NDC: 55714-1534 | Form: LIQUID
Manufacturer: Newton Laboratories, Inc.
Category: homeopathic | Type: HUMAN OTC DRUG LABEL
Date: 20250128

ACTIVE INGREDIENTS: GINGER 15 [hp_X]/1 mL; ECHINACEA, UNSPECIFIED 6 [hp_X]/1 mL; ARSENIC TRIOXIDE 15 [hp_X]/1 mL; ANTIMONY TRISULFIDE 15 [hp_X]/1 mL; SILVER NITRATE 15 [hp_X]/1 mL; BISMUTH 15 [hp_X]/1 mL; BRYONIA ALBA ROOT 15 [hp_X]/1 mL; MATRICARIA CHAMOMILLA 15 [hp_X]/1 mL; CINCHONA OFFICINALIS BARK 15 [hp_X]/1 mL; IRIS VERSICOLOR ROOT 15 [hp_X]/1 mL; POTASSIUM DICHROMATE 15 [hp_X]/1 mL; LACHESIS MUTA VENOM 15 [hp_X]/1 mL; LYCOPODIUM CLAVATUM SPORE 15 [hp_X]/1 mL; MAGNESIUM CARBONATE 15 [hp_X]/1 mL; STRYCHNOS NUX-VOMICA SEED 15 [hp_X]/1 mL; PHOSPHORUS 15 [hp_X]/1 mL; TOXICODENDRON PUBESCENS LEAF 15 [hp_X]/1 mL; PODOPHYLLUM 15 [hp_X]/1 mL; ANEMONE PULSATILLA 15 [hp_X]/1 mL; RADISH 15 [hp_X]/1 mL; TOBACCO LEAF 15 [hp_X]/1 mL; BAPTISIA TINCTORIA ROOT 15 [hp_X]/1 mL; JUGLANS REGIA LEAF 6 [hp_X]/1 mL; VERBASCUM THAPSUS 15 [hp_X]/1 mL
INACTIVE INGREDIENTS: WATER; ALCOHOL

Bowel 1534L

INDICATIONS & USAGE SECTION

Formulated for associated symptoms such as vomiting, burning, bloating, gas, nausea, cramping and pressure.

DOSAGE & ADMINISTRATION SECTION

Directions: Children, ages 0 to 11, give 3 drops by mouth (ages 12 and up, give 6 drops) 15 minutes before meals, as needed or as directed by a health professional. Sensitive persons begin with 1 drop and gradually increase to full dose.

OTC - ACTIVE INGREDIENT SECTION

Equal parts of Echinacea 6x, Juglans regia 6x, Antimonium crudum 15x, Argentum nitricum 15x, Arsenicum album 15x, Baptisia tinctoria 15x, Bismuthum metallicum 15x, Bryonia 15x, Chamomilla 15x, Cinchona officinalis 15x, Iris versicolor 15x, Kali bichromicum 15x, Lachesis mutus 15x, Lycopodium clavatum 15x, Magnesia carbonica 15x, Nux vomica 15x, Phosphorus 15x, Podophyllum peltatum 15x, Pulsatilla 15x, Raphanus sativus 15x, Rhus toxicodendron 15x, Tabacum 15x, Verbascum thapsus15x, Zingiber officinale 15x

OTC - PURPOSE SECTION

Formulated for associated symptoms such as vomiting, burning, bloating, gas, nausea, cramping and pressure.

INACTIVE INGREDIENT SECTION

Inactive Ingredients: USP Purified Water; USP Gluten-free, non-GMO, organic cane alcohol 20%.

QUESTIONS SECTION

newtonlabs.net – Questions? 800.448.7256

Newton Laboratories, Inc. FDA Est # 1051203 - Conyers, GA 30013

WARNINGS SECTION

WARNINGS: Keep out of reach of children. Do not use if tamper-evident seal is broken or missing. If symptoms worsen or persist for more than a few days, consult a doctor. If pregnant or breast-feeding, ask a doctor before use.

OTC - PREGNANCY OR BREAST FEEDING SECTION

If pregnant or breast-feeding, ask a doctor before use.

OTC - KEEP OUT OF REACH OF CHILDREN SECTION

Keep out of reach of children.